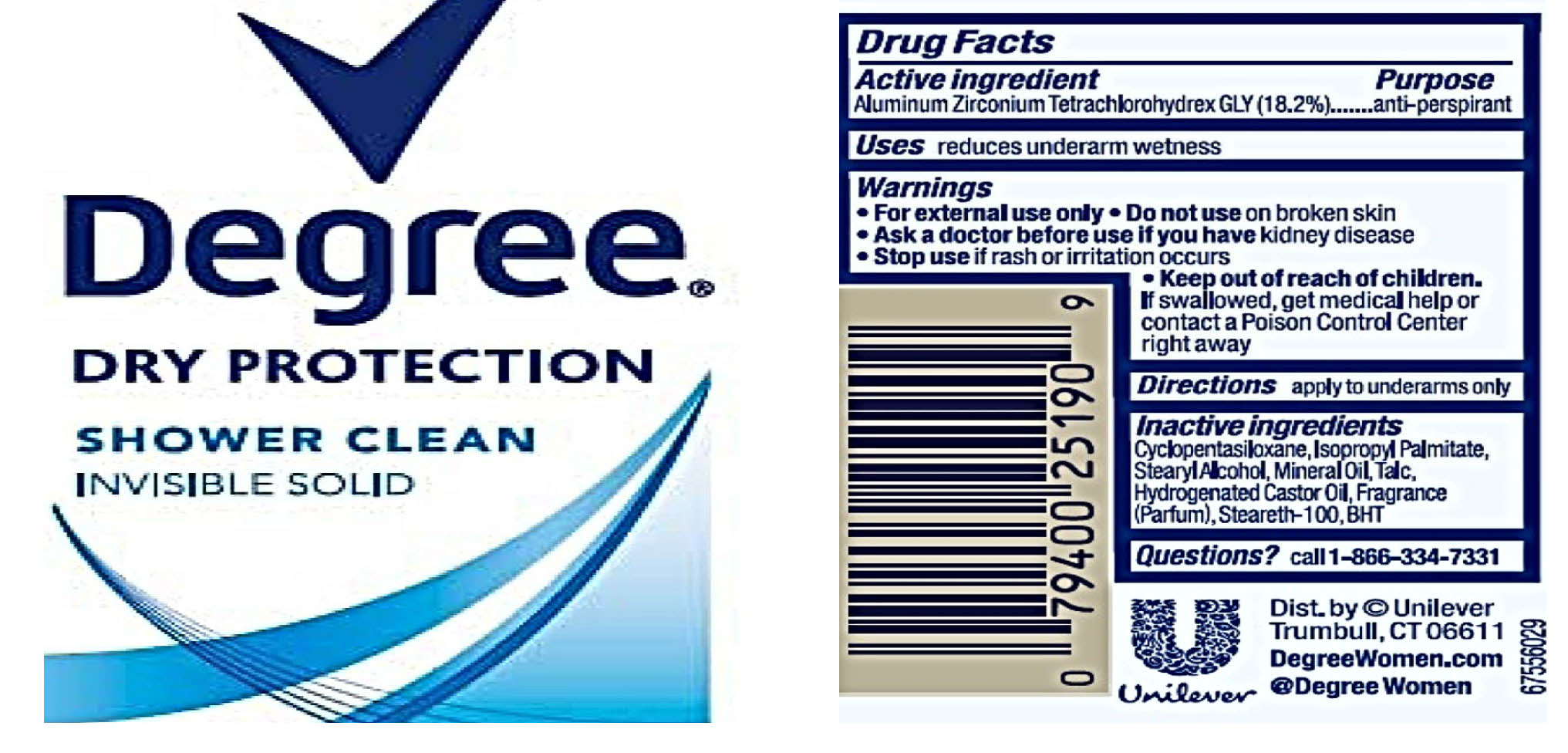 DRUG LABEL: Degree
NDC: 64942-1603 | Form: STICK
Manufacturer: Conopco Inc. d/b/a/ Unilever
Category: otc | Type: HUMAN OTC DRUG LABEL
Date: 20221207

ACTIVE INGREDIENTS: ALUMINUM ZIRCONIUM TETRACHLOROHYDREX GLY 18.2 g/100 g
INACTIVE INGREDIENTS: MINERAL OIL; STEARETH-100; HYDROGENATED CASTOR OIL; ISOPROPYL PALMITATE; TALC; CYCLOMETHICONE 5; BUTYLATED HYDROXYTOLUENE; STEARYL ALCOHOL

Degree Dry Protection Shower Clean Invisible Solid Antiperspirant & Deodorant

DEGREE DRY PROTECTION SHOWER CLEAN INVISIBLE SOLID ANTIPERSPIRANT & DEODORANT - aluminum zirconium tetrachlorohydrex gly stick

Degree Dry Protection Shower Clean Invisible Solid Antiperspirant & Deodorant

Drug Facts

Active ingredient

Aluminum Zirconium Tetrachlorohydrex GLY (18.2 %)

Purpose

antiperspirant

Uses

reduces underarm wetness

Warnings

• For external use only.
• Do not use on broken skin .
• Ask a doctor before use if you have kidney disease.
• Stop use if rash or irritation occurs.

• Keep out of reach of children.

If swallowed, get medical help or contact a Poison Control Center right away.

Directions

apply to underarms only

Inactive ingredients

Cyclopentasiloxane, Isopropyl Palmitate, Stearyl Alcohol, Mineral Oil, Talc, Hydrogenated Castor Oil, Fragrance (Parfum), Steareth-100, BHT.

Questions?

Call toll-free 1-866-334-7331